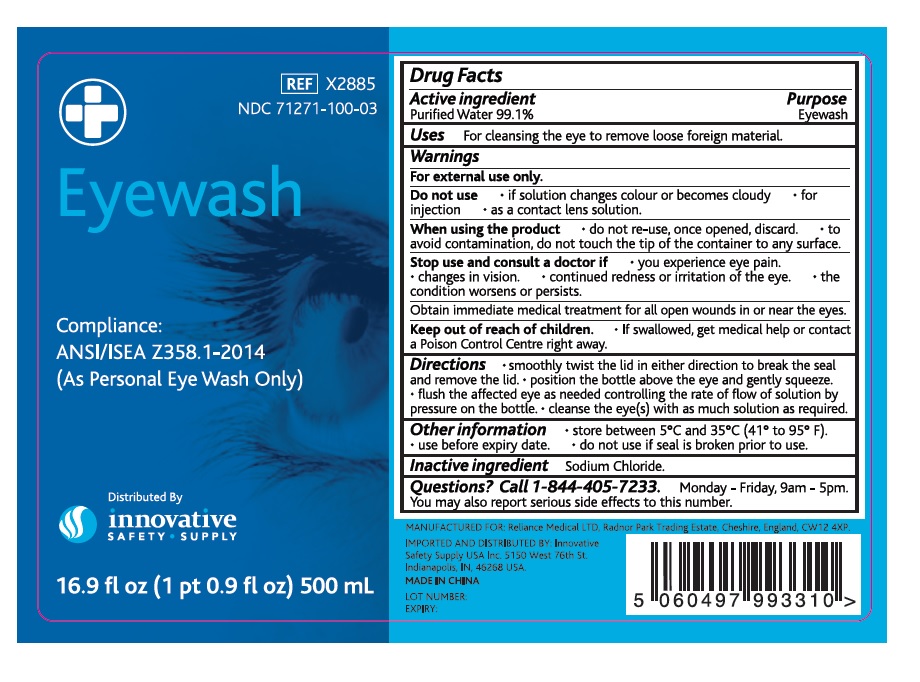 DRUG LABEL: Eyewash
NDC: 71271-100 | Form: LIQUID
Manufacturer: Reliance Medical Ltd
Category: otc | Type: HUMAN OTC DRUG LABEL
Date: 20180109

ACTIVE INGREDIENTS: WATER 0.991 mL/1 mL
INACTIVE INGREDIENTS: SODIUM CHLORIDE

Eyewash

Active ingredient

Purified Water 99.1 %

Purpose

Eyewash

Uses

For cleansing the eye to remove loose foreign material.

Warnings

For external use only.

Do not use • if solution changes colour or becomes cloudy • for injection • as a contact lens solution.

When using the product • do not re-use, once opened, discard. • to avoid contamination, do not touch the tip of the container to any surface.

Stop use and consult a doctor if • you experience eye pain. • changes in vision. • continued redness or irritation of the eye. • the
condition worsens or persists.

Obtain immediate medical treatment for all open wounds in or near the eyes.

Keep out of reach of children. • If swallowed, get medical help or contact a Poison Control Centre right away.

Directions

• smoothly twist the lid in either direction to break the seal and remove the lid. • position the bottle above the eye and gently squeeze.
• flush the affected eye as needed controlling the rate of flow of solution by pressure on the bottle. • cleanse the eye(s) with as much solution as required.

Other information

• store between 5°C and 35°C (41° to 95° F). • use before expiry date. • do not use if seal is broken prior to use.

Inactive ingredient

Sodium Chloride.

Questions?

Call 1-844-405-7233. Monday - Friday, 9am - 5pm. You may also report serious side effects to this number.

MANUFACTURED FOR:

Reliance Medical LTD, Radnor Park Trading

Estate, Congleton, Cheshire, England, CW12 4XP.

IMPORTED AND DISTRIBUTED BY:

Innovative Safety Supply USA Inc. 5150 West 76th St. Indianapolis,

IN, 46268 USA.

MADE IN CHINA

Compliance:

ANSI/ISEA Z358.1-2014

(As Personal Eye Wash Only)